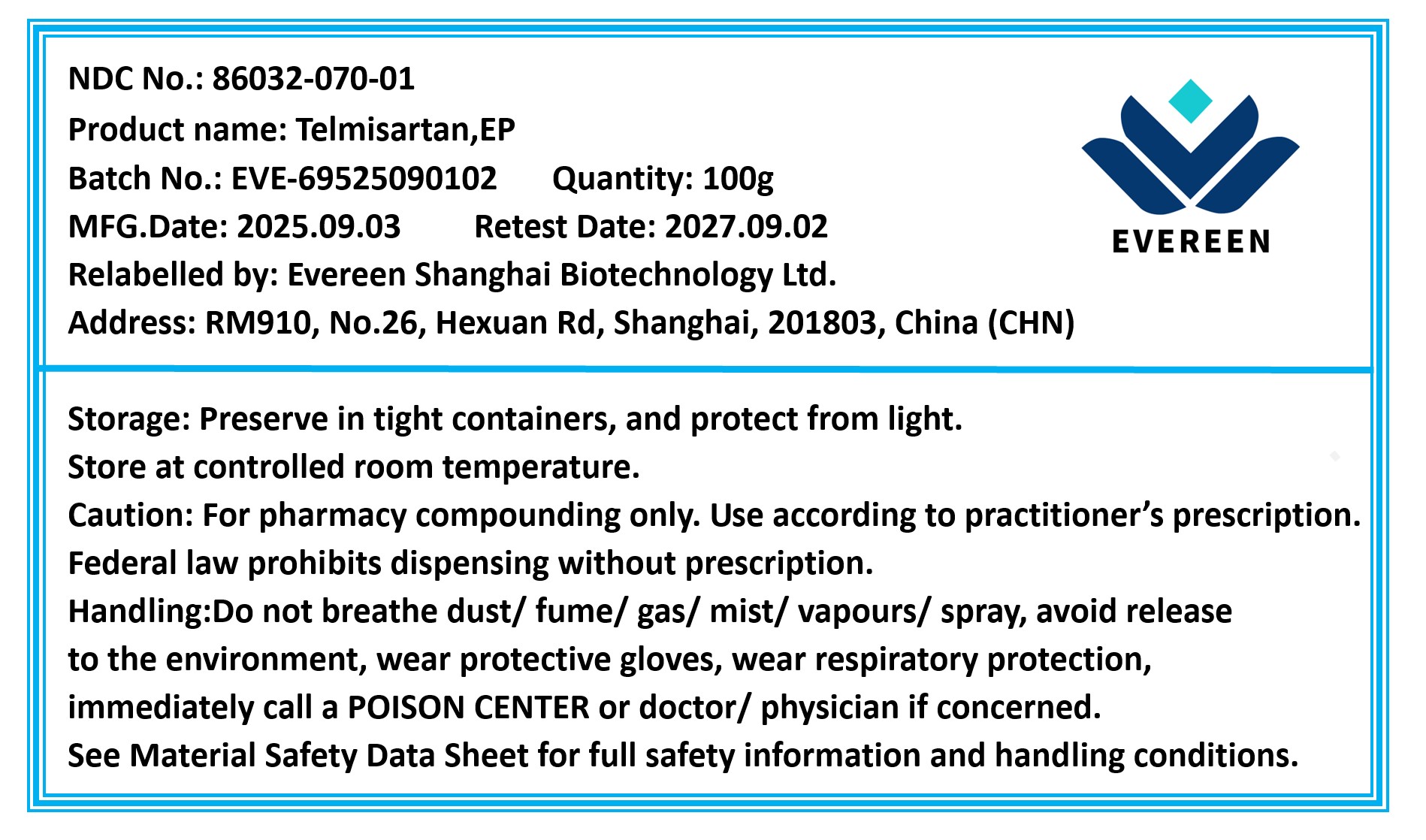 DRUG LABEL: Telmisartan
NDC: 86032-070 | Form: POWDER
Manufacturer: Evereen Shanghai Biotechnology Ltd.
Category: other | Type: BULK INGREDIENT - ANIMAL DRUG
Date: 20260203

ACTIVE INGREDIENTS: TELMISARTAN 1 g/1 g

Telmisartan